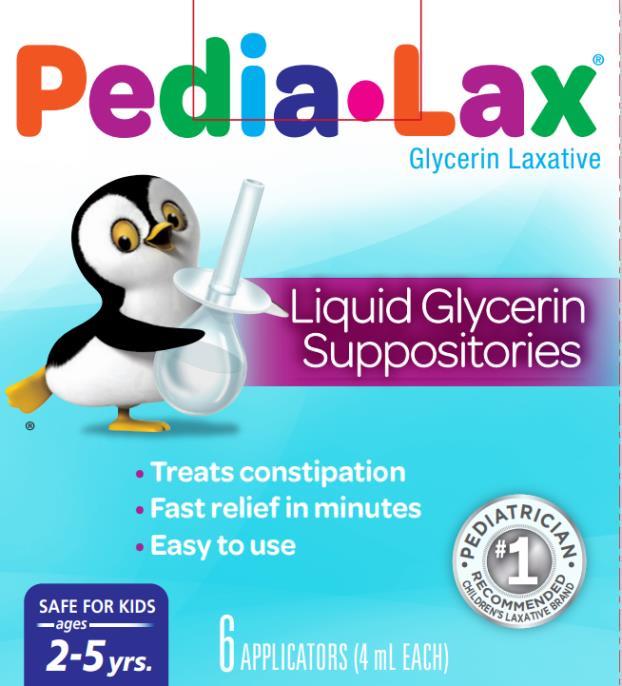 DRUG LABEL: Pedia-Lax
NDC: 0132-0190 | Form: LIQUID
Manufacturer: C.B. Fleet Company, Inc.
Category: otc | Type: HUMAN OTC DRUG LABEL
Date: 20241223

ACTIVE INGREDIENTS: GLYCERIN 2.8 g/2.7 mL
INACTIVE INGREDIENTS: WATER; EDETATE DISODIUM

Pedia-Lax Glycerin Liquid

Active Ingredient (in each 2.7 mL average delivered dose)

Glycerin 2.8 g

Purpose

Hyperosmotic Laxative

Uses

- for relief of occasional constipation
- this product usually produces bowel movement in 1/4 to 1 hour

Warnings

For rectal use only.

May cause rectal discomfort or a burning sensation.

Ask a doctor before using any laxative if the child has

- abdominal pain, nausea or vomiting
- a sudden change in bowel habits lasting more than 2 weeks
- already used a laxative for more than 1 week
- if constipation continues after one week of use, contact your child's doctor

Stop using this product and consult a doctor if the child has

- rectal bleeding
- no bowel movement within 1 hour of using this product

These symptoms may indicate a serious condition.

Keep out of reach of children.

If swallowed, get medical help or contact a Poison Control Center (1-800-222-1222) right away.

Directions

Single Daily Dosage (per 24 hours)

children 2 to under 6 years | 1 suppository per day or as directed by a doctor
children under 2 years | consult a doctor

Administering the laxative:
CAUTION: REMOVE ORANGE PROTECTIVE SHIELD BEFORE INSERTING. Hold unit upright, grasping bulb of unit with fingers. Grasp orange protective shield with other hand, pull gently to remove. With steady pressure, gently insert tip into rectum with slight side-to-side movement, with tip pointing toward navel. Discontinue use if resistance is encountered. Forcing the tip can result in injury. Insertion may be easier if child receiving suppository bears down as if having a bowel movement. This helps relax the muscles around the anus. Squeeze the bulb until nearly all liquid is expelled. While continuing to squeeze the bulb, remove tip from rectum and discard unit. It is not necessary to empty unit completely. The unit contains more than the amount of liquid needed for effective use. A small amount of liquid will remain in the unit after squeezing.

Left-side position: Place child on left side with knees bent and arms resting comfortably.

Knee-chest position: Have child kneel, then lower head and chest forward until left side of face is resting on surface with left arm folded comfortably.

Other Information

Carton sealed for safety. If seal with Fleet emblem on bottom flap or top flap is broken or missing, do not use.

Inactive Ingredients

edetate disodium, purified water

Questions ?

1-866-255-6960 or www.pedia-lax.com

PRINCIPAL DISPLAY PANEL

Pedia-Lax®
Glycerin Laxative
Liquid Glycerin Suppositories
6 APPLICATORS
(4 mL EACH)